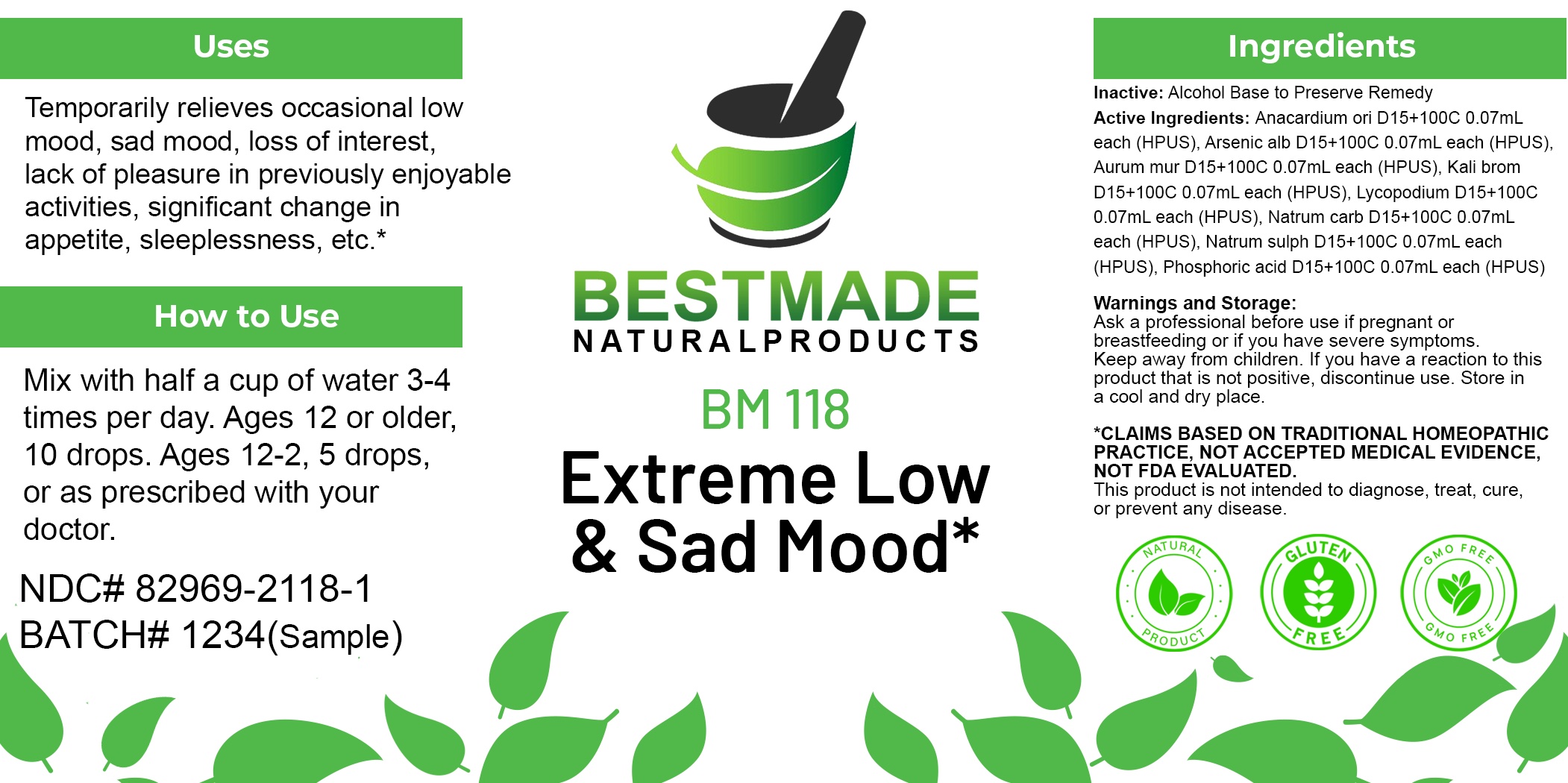 DRUG LABEL: Bestmade Natural Products BM118
NDC: 82969-2118 | Form: LIQUID
Manufacturer: Bestmade Natural Products
Category: homeopathic | Type: HUMAN OTC DRUG LABEL
Date: 20250207

ACTIVE INGREDIENTS: POTASSIUM BROMIDE 30 [hp_C]/30 [hp_C]; SODIUM CARBONATE 30 [hp_C]/30 [hp_C]; GOLD TRICHLORIDE 30 [hp_C]/30 [hp_C]; ARSENIC TRIOXIDE 30 [hp_C]/30 [hp_C]; PHOSPHORIC ACID 30 [hp_C]/30 [hp_C]; SODIUM SULFATE 30 [hp_C]/30 [hp_C]; SEMECARPUS ANACARDIUM JUICE 30 [hp_C]/30 [hp_C]; LYCOPODIUM CLAVATUM SPORE 30 [hp_C]/30 [hp_C]
INACTIVE INGREDIENTS: ALCOHOL 30 [hp_C]/30 [hp_C]

BM118

DOSAGE AND ADMINISTRATION

How to Use

Mix with half a cup of water 3-4 times per day. Ages 12 or older, 10 drops. Ages 12-2, 5 drops. Ages 2 and under, consult your Doctor.

Inactive:

Alcohol Base to Preserve Product

ACTIVE INGREDIENT

ACTIVE INGREDIENTSAnacardium ori D15+100C 0.07mL each (HPUS), Arsenic alb D15+100C 0.07mL each (HPUS), Aurum mur D15+100C 0.07mL each (HPUS), Kali brom D15+100C 0.07mL each (HPUS), Lycopodium D15+100C 0.07mL each (HPUS), Natrum carb D15+100C 0.07mL each (HPUS), Natrum sulph D15+100C 0.07mL each (HPUS), Phosphoric acid D15+100C 0.07mL each (HPUS)

Uses
Temporarily relieves occasional low mood, sad mood, loss of interest, lack of pleasure in previously enjoyable activities, significant change in appetite, sleeplessness, etc.*

Uses
Temporarily relieves occasional low mood, sad mood, loss of interest, lack of pleasure in previously enjoyable activities, significant change in appetite, sleeplessness, etc.*

KEEP OUT OF REACH OF CHILDREN

Warnings and Storage:

Ask a professional before use if pregnant or breastfeeding or if you have severe symptoms.

Keep away from children. If you have a reaction to this product that is not positive, discontinue use. Store in a cool and dry place

*CLAIMS BASED ON TRADITIONAL HOMEOPATHIC PRACTICE, NOT ACCEPTED MEDICAL EVIDENCE NOT FDA EVALUATED.
This product is not intended to diagnose, treat, cure, or prevent any disease.

Warnings and Storage:

Ask a professional before use if pregnant or breastfeeding or if you have severe symptoms.

Keep away from children. If you have a reaction to this product that is not positive, discontinue use. Store in a cool and dry place

*CLAIMS BASED ON TRADITIONAL HOMEOPATHIC PRACTICE, NOT ACCEPTED MEDICAL EVIDENCE NOT FDA EVALUATED.
This product is not intended to diagnose, treat, cure, or prevent any disease.

Entire package label